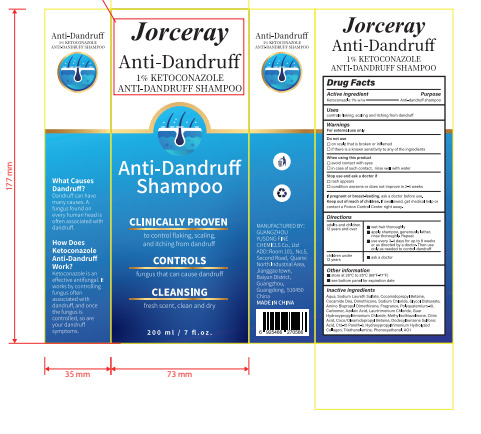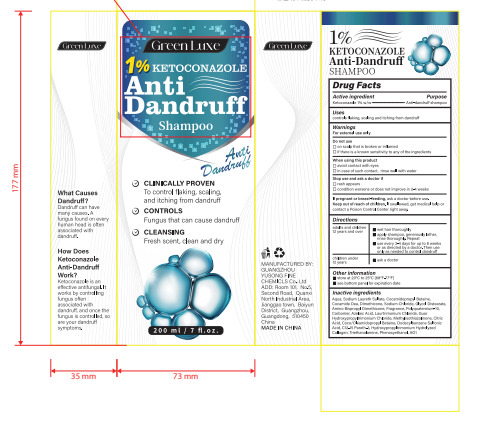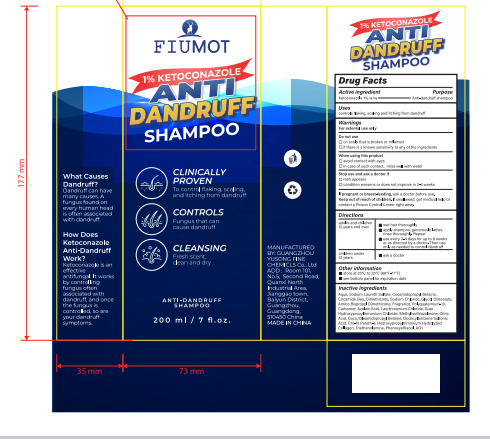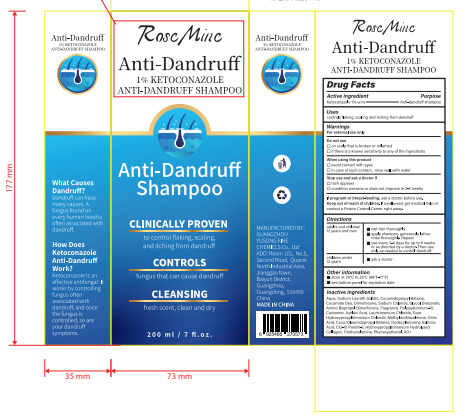 DRUG LABEL: 1% ketoconazole anti dandruff
NDC: 84558-005 | Form: SHAMPOO
Manufacturer: GUANGZHOU YUSONG FINE CHEMICLS Co., Ltd
Category: otc | Type: HUMAN OTC DRUG LABEL
Date: 20241203

ACTIVE INGREDIENTS: KETOCONAZOLE 1 g/100 mL
INACTIVE INGREDIENTS: DODECYLBENZENESULFONIC ACID; AQUA; SODIUM LAURETH SULFATE; COCAMIDOPROPYL BETAINE; COCAMIDE DEA; DIMETHICONE; SODIUM CHLORIDE; GLYCOL DISTEARATE; CARBOMER; AZELAIC ACID; LAURTRIMONIUM CHLORIDE; GUAR HYDROXYPROPYLTRIMONIUM CHLORIDE; METHYLISOTHIAZOLINONE; CITRIC ACID; C12-15 PARETH-3; COCO/OLEAMIDOPROPYL BETAINE; TRIETHANOLAMINE; FD&C BLUE NO. 1; PHENOXYETHANOL

Active Ingredient(s)

Ketoconazole 1%

Purpose

Anti-dandruff shampoo

Use

controls flaking, scaling and itching from dandruff

Warnings

For external use only

Do not use

on scalp that is broken or inflamed

if there is a known sensitivity to any of the ingredients

WHEN USING

avoid contact with eyes
in case of such contact, rinse well with water

STOP USE

rash appears
condition worsens or does not improve in 2-4 weeks

Keep out of reach of children. If swallowed, get medical help or
contact a Poison Control Center right away,

Directions

adults and children 12 years and over：①wet hair thoroughly ②apply shampoo, generously lather, rinse thoroughly. Repeat
③use every 3-4 days for up to 8 weeks or as directed by a doctor,' Then use only as needed to control dandruff

children under 12 years： ask a doctor

Other information

①store at 20°C to 25°C (68*F-77°F)
②see bottom panel for expiration date

Inactive ingredients

Aqua, Sodium Laureth Sulfate, Cocamidopropyl Betaine, Cocamide Dea, Dimethicone, Sodium Chloride, Glycol Distearate,
Amino BispropyI Dimethicone, Fragrance, Polyquaternium-10, Carbomer, Azelaic Acid, L aurtrimonium Chloride, Guar
Hydroxypropyltrimonium Chloride, Methylisothiazolinone, Citric Acid, Coco/Oleamidopropyl Betaine, Dodecylbenzene Sulfonic
Acid, C12-15 Pareth-3, Hydroxypropyltrimonium Hydrolyzed Collagen, Triethanolamine, Phenoxyethanol, AO1